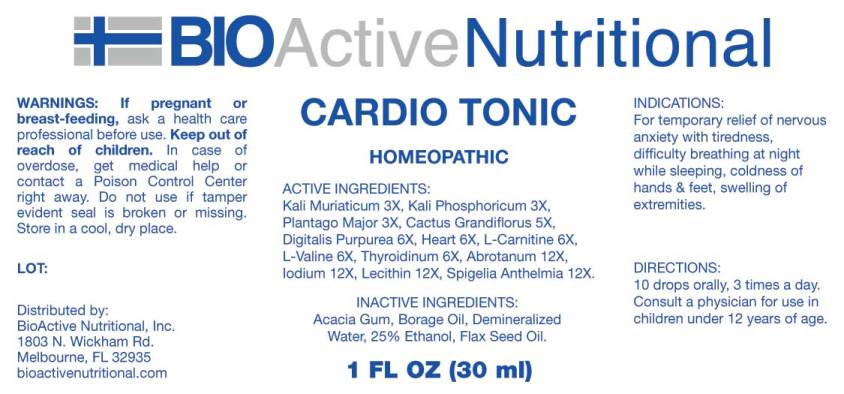 DRUG LABEL: Cardio Tonic
NDC: 43857-0073 | Form: LIQUID
Manufacturer: BioActive Nutritional, Inc.
Category: homeopathic | Type: HUMAN OTC DRUG LABEL
Date: 20170814

ACTIVE INGREDIENTS: POTASSIUM CHLORIDE 3 [hp_X]/1 mL; POTASSIUM PHOSPHATE, DIBASIC 3 [hp_X]/1 mL; PLANTAGO MAJOR 3 [hp_X]/1 mL; SELENICEREUS GRANDIFLORUS STEM 5 [hp_X]/1 mL; DIGITALIS 6 [hp_X]/1 mL; BEEF HEART 6 [hp_X]/1 mL; LEVOCARNITINE 6 [hp_X]/1 mL; VALINE 6 [hp_X]/1 mL; SUS SCROFA THYROID 6 [hp_X]/1 mL; ARTEMISIA ABROTANUM FLOWERING TOP 12 [hp_X]/1 mL; IODINE 12 [hp_X]/1 mL; EGG PHOSPHOLIPIDS 12 [hp_X]/1 mL; SPIGELIA ANTHELMIA 12 [hp_X]/1 mL
INACTIVE INGREDIENTS: BORAGE OIL; LINSEED OIL; ACACIA; WATER; ALCOHOL

Drug Facts:

ACTIVE INGREDIENTS:

Kali Muriaticum 3X, Kali Phosphoricum 3X, Plantago Major 3X, Cactus Grandiflorus 5X, Digitalis Purpurea 6X, Heart (Bovine) 6X, L-Carnitine 6X, L-Valine 6X, Thyroidinum (Suis) 6X, Abrotanum (Artemisia Abrotanum) 12X, Iodium 12X, Lecithin 12X, Spigelia Anthelmia 12X.

INDICATIONS:

For temporary relief of nervous anxiety with tiredness, difficulty breathing at night while sleeping, coldness of hands & feet, swelling of extremities.

WARNINGS:

If pregnant or breast-feeding, ask a health care professional before use.

Keep out of reach of children. In case of overdose, get medical help or contact a Poison Control Center right away.

Do not use if tamper evident seal is broken or missing.

Store in cool, dry place.

DIRECTIONS:

10 drops orally, 3 times a day. Consult a physician for use in children under 12 years of age.

INACTIVE INGREDIENTS:

Acacia Gum, Borage Oil, Demineralized Water, 25% Ethanol, Flax Seed Oil

Keep out of reach of children. In case of overdose, get medical help or contact a Poison Control Center right away.

INDICATIONS:

For temporary relief of nervous anxiety with tiredness, difficulty breathing at night while sleeping, coldness of hands & feet, swelling of extremities.

QUESTIONS:

Distributed by:
BioActive Nutritional, Inc.
1803 N. Wickham Rd.
Melbourne, FL 32935
bioactivenutritional.com

PACKAGE LABEL DISPLAY:

BIOActive Nutritional

CARDIO TONIC

HOMEOPATHIC

1 FL OZ (30 ml)